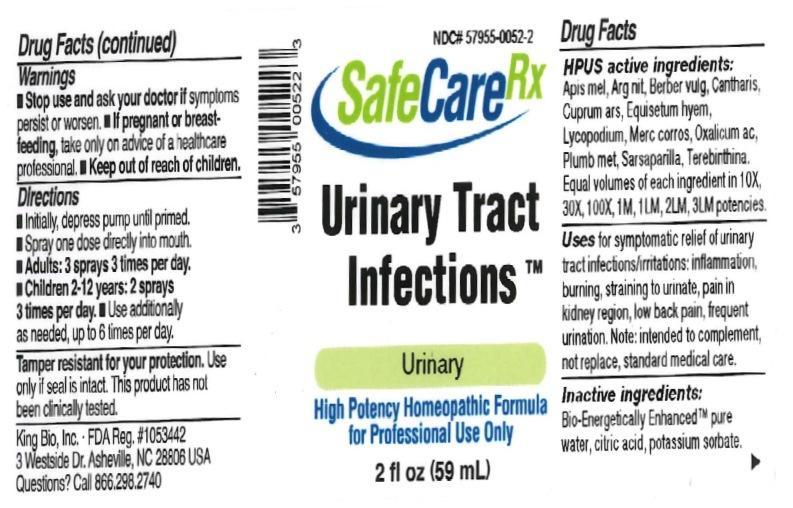 DRUG LABEL: Urinary Tract Infections
NDC: 57955-0052 | Form: LIQUID
Manufacturer: King Bio Inc.
Category: homeopathic | Type: HUMAN OTC DRUG LABEL
Date: 20161110

ACTIVE INGREDIENTS: APIS MELLIFERA 10 [hp_X]/59 mL; SILVER NITRATE 10 [hp_X]/59 mL; BERBERIS VULGARIS ROOT BARK 10 [hp_X]/59 mL; LYTTA VESICATORIA 10 [hp_X]/59 mL; CUPRIC ARSENITE 10 [hp_X]/59 mL; EQUISETUM HYEMALE 10 [hp_X]/59 mL; LYCOPODIUM CLAVATUM SPORE 10 [hp_X]/59 mL; MERCURIC CHLORIDE 10 [hp_X]/59 mL; OXALIC ACID DIHYDRATE 10 [hp_X]/59 mL; LEAD 10 [hp_X]/59 mL; SMILAX REGELII ROOT 10 [hp_X]/59 mL; TURPENTINE OIL 10 [hp_X]/59 mL
INACTIVE INGREDIENTS: WATER; ANHYDROUS CITRIC ACID; POTASSIUM SORBATE

Urinary Tract Infections™

ACTIVE INGREDIENT

Drug Facts__________________________________________________________________________________________________________

HPUS active ingredients: Apis mellifica, Argentum nitricum, Berberis vulgaris, Cantharis, Cuprum arsenicosum, Equisetum hyemale, Lycopodium clavatum, Mercurius corrosivus, Oxalicum acidum, Plumbum metallicum, Sarsaparilla, Terebinthina. Equal volumes of each ingredient in 10X, 30X, 100X, 1M, 1LM, 2LM, 3LM potencies.

INDICATIONS AND USAGE

Uses for symptomatic relief of urinary tract infections/irritations: inflammation, burning, straining to urinate, pain in kidney region, low back pain, and frequent urination. Note: intended to complement, not replace, standard medical care.

INACTIVE INGREDIENT

Inactive Ingredients: Bio-Energetically Enhanced™ pure water, citric acid and potassium sorbate.

Warnings

- Stop use and ask your doctor if symptoms persist or worsen.
- If pregnant or breast-feeding, take only on advice of a healthcare professional.

- Keep out of reach of children.

Directions

- Initially, depress pump until primed.
- Spray one dose directly into mouth.
- Adults: 3 sprays 3 times per day.
- Children 2-12 years: 2 sprays 3 times per day.
- Use additionally as needed, up to 6 times per day.

OTHER SAFETY INFORMATION

Tamper resistant for your protection. Use only if safety seal is intact. This product has not been clinically tested.

PURPOSE

Uses for symptomatic relief of urinary tract infections/irritations:

- inflammation
- burning
- straining to urinate
- pain in kidney region
- low back pain
- frequent urination
- Note: intended to complement, not replace, standard medical care.